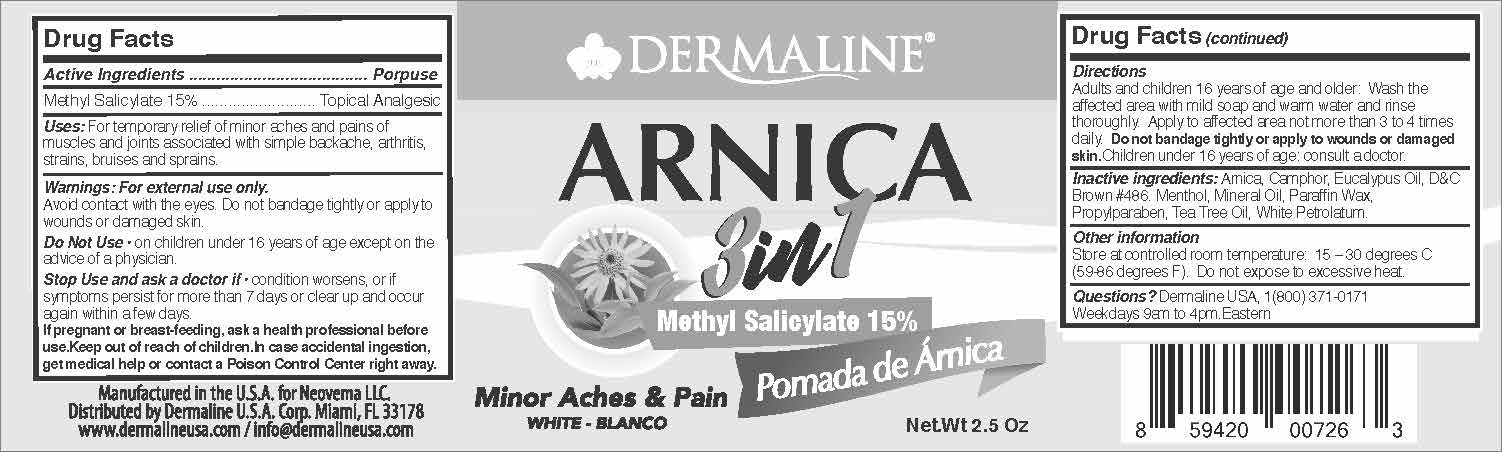 DRUG LABEL: Topical Analgesic
NDC: 82165-101 | Form: OINTMENT
Manufacturer: Dermaline USA Corp
Category: otc | Type: HUMAN OTC DRUG LABEL
Date: 20230214

ACTIVE INGREDIENTS: METHYL SALICYLATE 15 mg/100 g
INACTIVE INGREDIENTS: PROPYLPARABEN; WHITE PETROLATUM; CAMPHOR (SYNTHETIC); WATER; ARNICA MONTANA; EUCALYPTUS OIL; MENTHOL; MINERAL OIL; PARAFFIN; TEA TREE OIL

Dermaline Arnica 3 in 1

Active Ingredient(s)

Methyl Salicylate 15% . Purpose: Topical Analgesic

Purpose

Topical Analgesic

Use

For temporary relief of minor aches and pains of muscles and joints associated with simple backache, arthritis, strains, bruises and sprains.

Warnings

For external use only. Avoid Contact with the eyes. Do not bandage tightly or apply to wounds or damaged costs.

Do not use

- On children under 16 years of age except on the advice of the physician.

Keep out of reach of children. If swallowed, get medical help or contact a Poison Control Center right away.

PREGNANCY

If pregnant or breast-feeding, ask a health professional before use. Keep out of reach of children. In case accidental ingestion, get medical help or contact a Poision Control Center right away.

Directions

Adults and children 16 years of age and older: Wash the affected area with mild soap and warm water and rinse thoroughly. Apply to affected area not more than 3 to 4 times daily.

Do not bandage tightly or apply to wounds or damaged skin. Children under 16 years of age; consult a doctor.

Other information

- Store between 15-30C (59-86F)
- Avoid freezing and excessive heat

Inactive ingredients

Arnica, camphor, eucalyptus oil, D&C brown #486. Menthol, Mineral Oil, Paraffin Wax, Propylparaben, Tea Tree Oil, White Petrolatum

STOP USE

condition worsens, or if symptoms persist for more than 7 days or clear up and occur again with a few days.

Package Label - Principal Display Panel

2.5oz